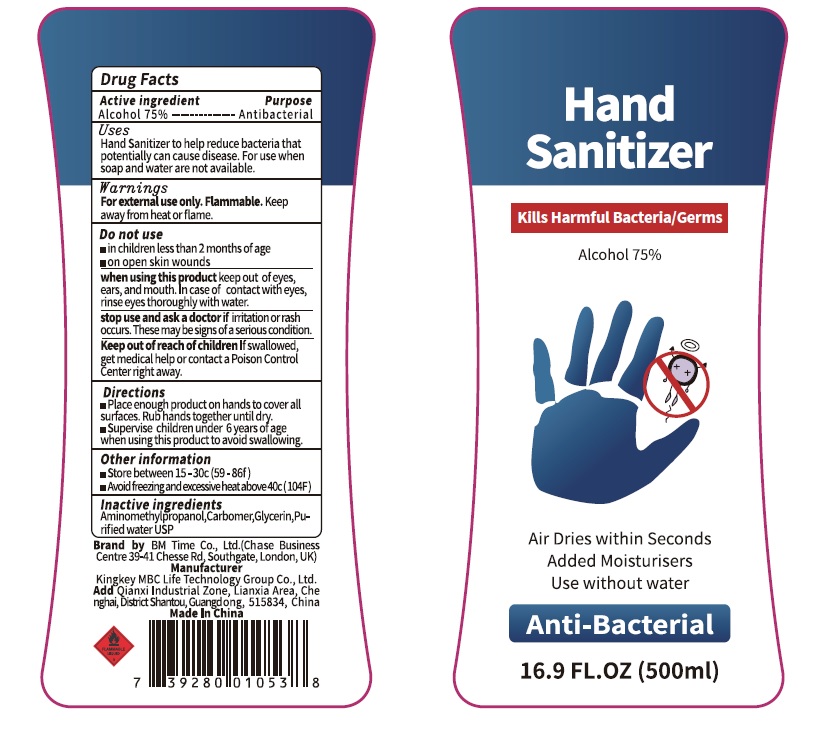 DRUG LABEL: HAND SANITIZER
NDC: 73928-002 | Form: LIQUID
Manufacturer: KINGKEY MBC LIFE TECHNOLOGY GROUP CO., LTD
Category: otc | Type: HUMAN OTC DRUG LABEL
Date: 20251007

ACTIVE INGREDIENTS: ALCOHOL 75 mL/100 mL
INACTIVE INGREDIENTS: AMINOMETHYLPROPANOL; WATER; CARBOMER 980; GLYCERIN

Hand sanitizer

Active Ingredient

Alcohol

Purpose

Antibacterial

Uses

Hand Sanitizer to help reduce bacteria that potentially can cause disease.

For use when soap and water are not available.

Warnings

For external use only. Flammable. Keep away from heat or flame.

Do not use

- in children less than 2 months of age
- on open skin wounds .

when using this product

- keep out of eyes, ears, and mouth.
- In case of contact with eyes, rinse eyes thoroughly with water.

stop use and ask a doctor

- if irritation or rash occurs. These may be signs of a serious condition. Keep out of reach of children
- If swallowed, get medical help or contact a Poison Control Center right away.

Directions

- Place enough product on hands to cover all surfaces. Rubhands together until dry.
- Supervise children under 6 years of age when using this product to avoid swallowing.

Keep Out Of Reach Of Childrens

Keep out of reach of children If swallowed, get medical help or contact a Poison Control Center right

Other information

Store between 15-30C (59-86f)
Avoid freezing and excessive heat above 40c(104F)

Inactive ingredients

Aminomethylpropanol, Carbomer,Glycerin,Water